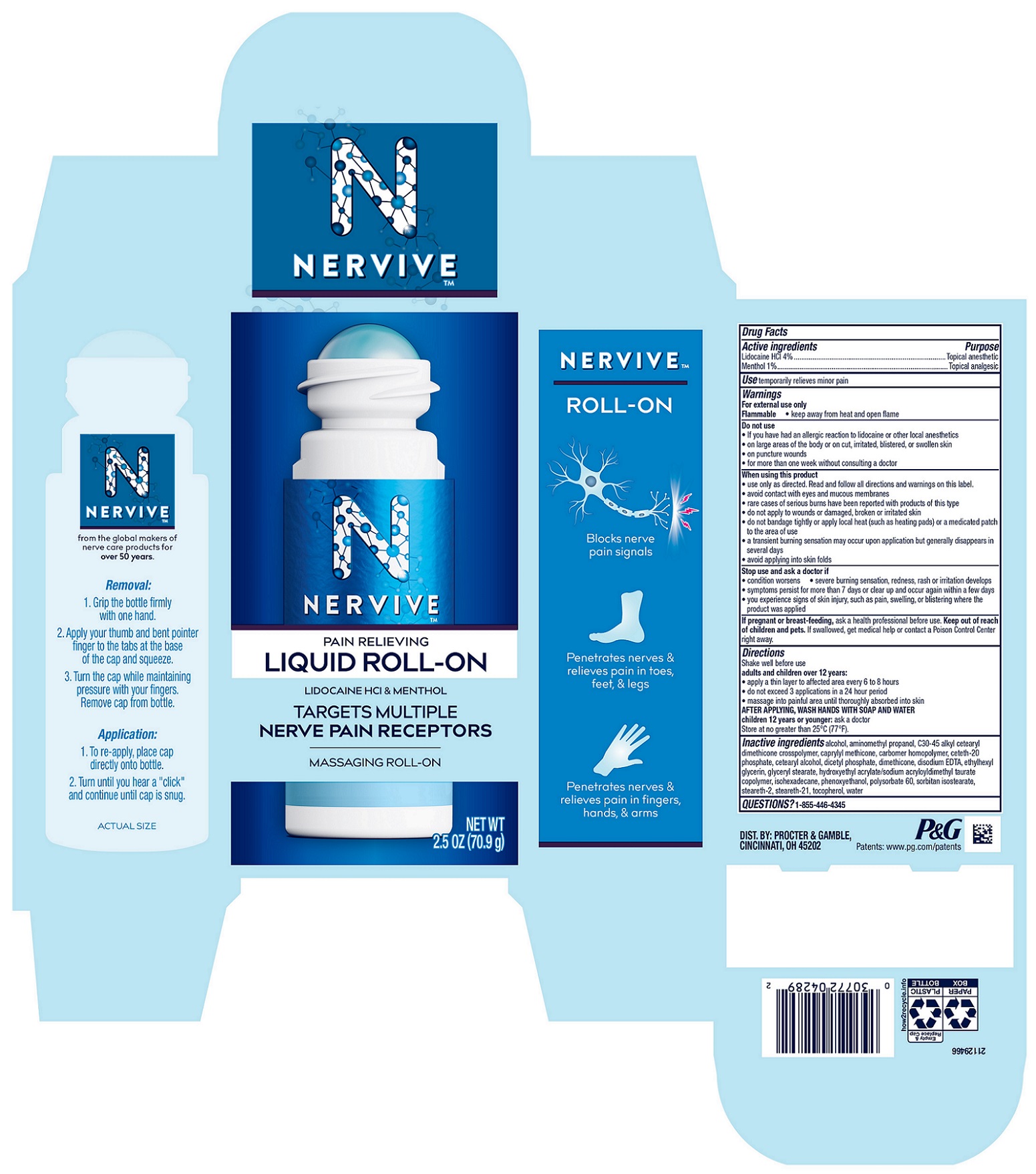 DRUG LABEL: Nervive Pain Relieving
NDC: 84126-317 | Form: LIQUID
Manufacturer: The Procter & Gamble Manufacturing Company
Category: otc | Type: HUMAN OTC DRUG LABEL
Date: 20251003

ACTIVE INGREDIENTS: LIDOCAINE HYDROCHLORIDE ANHYDROUS 4 g/100 g; MENTHOL 1 g/100 g
INACTIVE INGREDIENTS: DIMETHICONE; CAPRYLYL TRISILOXANE; CARBOMER INTERPOLYMER TYPE B (ALLYL PENTAERYTHRITOL CROSSLINKED); AMINOMETHYLPROPANOL; PHENOXYETHANOL; STEARETH-21; HYDROXYETHYL ACRYLATE/SODIUM ACRYLOYLDIMETHYL TAURATE COPOLYMER (45000 MPA.S AT 1%); ISOHEXADECANE; ETHYLHEXYLGLYCERIN; CETETH-20 PHOSPHATE; GLYCERYL MONOSTEARATE; ALCOHOL; CETOSTEARYL ALCOHOL; SORBITAN ISOSTEARATE; POLYSORBATE 60; TOCOPHEROL; C30-45 ALKYL CETEARYL DIMETHICONE CROSSPOLYMER; EDETATE DISODIUM; WATER; DIHEXADECYL PHOSPHATE; STEARETH-2

NERVIVE™ PAIN RELIEVING Liquid Roll-on

Drug Facts

Active ingredients

Lidocaine HCl 4%

Menthol 1%

Active ingredients Purpose

Topical anesthetic

Topical analgesic

Use

temporarily relieves minor pain

Warnings

For external use only
Flammable

- keep away from heat and open flame

Do not use

• If you have had an allergic reaction to lidocaine or other local anesthetics
• on large areas of the body or on cut, irritated, blistered, or swollen skin
• on puncture wounds
• for more than one week without consulting a doctor

When using this product

• use only as directed. Read and follow all directions and warnings on this carton.
• avoid contact with eyes and mucous membranes
• rare cases of serious burns have been reported with products of this type
• do not apply to wounds or damaged, broken or irritated skin
• do not bandage tightly or apply local heat (such as heating pads) or a medicated patch to the area of use
• a transient burning sensation may occur upon application but generally disappears in several days
• avoid applying into skin folds

Stop use and ask a doctor if

• condition worsens

• severe burning sensation, redness, rash or irritation develops

• symptoms persist for more than 7 days or clear up and occur again within a few days

• you experience signs of skin injury, such as pain, swelling, or blistering where the product was applied

If pregnant or breast-feeding,

ask a health professional before use.

Keep out of reach of children and pets.

OVERDOSAGE

If swallowed, get medical help or contact a Poison Control Center right away.

Directions

Shake well before use

adults and children over 12 years:

- apply a thin layer to affected area every 6 to 8 hours
- do not exceed 3 applications in a 24 hour period
- massage into painful area until thoroughly absorbed into skin

AFTER APPLYING, WASH HANDS WITH SOAP AND WATER
children 12 years or younger: ask a doctor

Store at no greater than 25°C (77°F).

Inactive ingredients

alcohol, aminomethyl propanol, C30-45 alkyl cetearyl dimethicone crosspolymer, caprylyl methicone, carbomer homopolymer, ceteth-20 phosphate, cetearyl alcohol, dicetyl phosphate, dimethicone, disodium EDTA, ethylhexyl glycerin, glyceryl stearate, hydroxyethyl acrylate/sodium acryloyldimethyl taurate copolymer, isohexadecane, phenoxyethanol, polysorbate 60, sorbitan isostearate, steareth-2, steareth-21, tocopherol, water

Questions?

1-855-446-4345

DIST. BY: PROCTER & GAMBLE, CINCINNATI, OH 45202

PRINCIPAL DISPLAY PANEL - 2.5 OZ

NERVIVE™

PAIN RELIEVING

LIQUID ROLL-ON

LIDOCAINE HCl & MENTHOL

TARGETS MULTIPLE

NERVE PAIN RECEPTORS

MASSAGING ROLL-ON

NET WT 2.5 OZ (70.9 g)